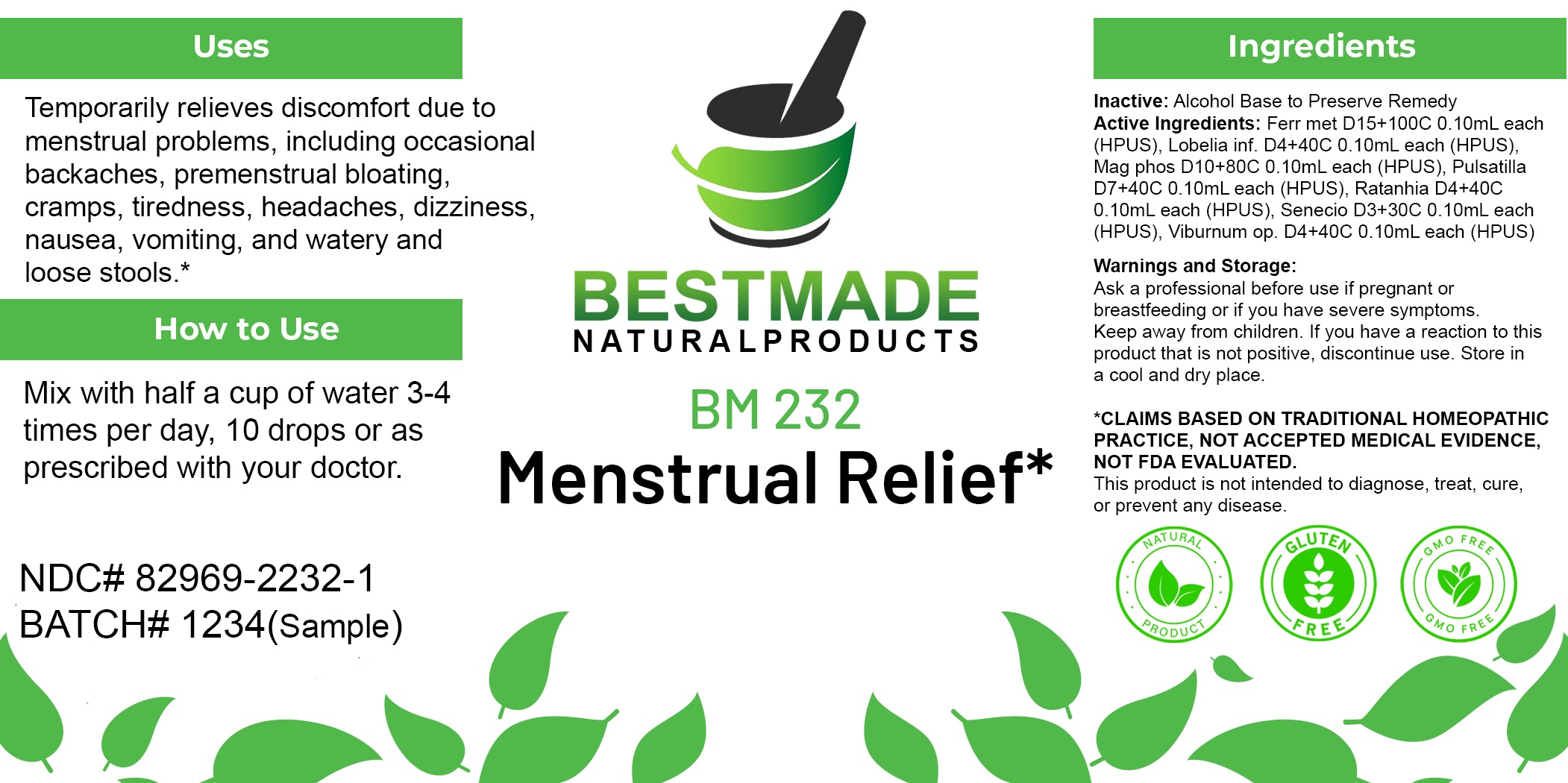 DRUG LABEL: Bestmade Natural Products BM232
NDC: 82969-2232 | Form: LIQUID
Manufacturer: Bestmade Natural Products
Category: homeopathic | Type: HUMAN OTC DRUG LABEL
Date: 20250304

ACTIVE INGREDIENTS: PACKERA AUREA 30 [hp_C]/30 [hp_C]; MAGNESIUM PHOSPHATE, DIBASIC TRIHYDRATE 30 [hp_C]/30 [hp_C]; KRAMERIA LAPPACEA ROOT 30 [hp_C]/30 [hp_C]; PULSATILLA VULGARIS 30 [hp_C]/30 [hp_C]; VIBURNUM OPULUS BARK 30 [hp_C]/30 [hp_C]; IRON 30 [hp_C]/30 [hp_C]; LOBELIA INFLATA 30 [hp_C]/30 [hp_C]
INACTIVE INGREDIENTS: ALCOHOL 30 [hp_C]/30 [hp_C]

BM232

DOSAGE AND ADMINISTRATION

How to Use

Mix with half a cup of water 3-4 times per day. Ages 12 or older, 10 drops. Ages 12-2, 5 drops. Ages 2 and under, consult your Doctor.

Inactive:

Alcohol Base to Preserve Product

ACTIVE INGREDIENT

Active Ingredients: Ferr met D15+100C 0.10mL each (HPUS), Lobelia inf. D4+40C 0.10mL each (HPUS), Mag phos D10+80C 0.10mL each (HPUS), Pulsatilla D7+40C 0.10mL each (HPUS), Ratanhia D4+40C 0.10mL each (HPUS), Senecio D3+30C 0.10mL each (HPUS), Viburnum op. D4+40C 0.10mL each (HPUS)

KEEP OUT OF REACH OF CHILDREN

Warnings and Storage:

Ask a professional before use if pregnant or breastfeeding or if you have severe symptoms.

Keep away from children. If you have a reaction to this product that is not positive, discontinue use. Store in a cool and dry place

*CLAIMS BASED ON TRADITIONAL HOMEOPATHIC PRACTICE, NOT ACCEPTED MEDICAL EVIDENCE NOT FDA EVALUATED.
This product is not intended to diagnose, treat, cure, or prevent any disease.

Warnings and Storage:

Ask a professional before use if pregnant or breastfeeding or if you have severe symptoms.

Keep away from children. If you have a reaction to this product that is not positive, discontinue use. Store in a cool and dry place

*CLAIMS BASED ON TRADITIONAL HOMEOPATHIC PRACTICE, NOT ACCEPTED MEDICAL EVIDENCE NOT FDA EVALUATED.
This product is not intended to diagnose, treat, cure, or prevent any disease.

Uses
Temporarily relieves discomfort due to menstrual problems, including occasional backaches, premenstrual bloating. cramps, tiredness, headaches, dizziness nausea, vomiting, and watery and loose stools.*

Uses
Temporarily relieves discomfort due to menstrual problems, including occasional backaches, premenstrual bloating. cramps, tiredness, headaches, dizziness nausea, vomiting, and watery and loose stools.*

Entire package label